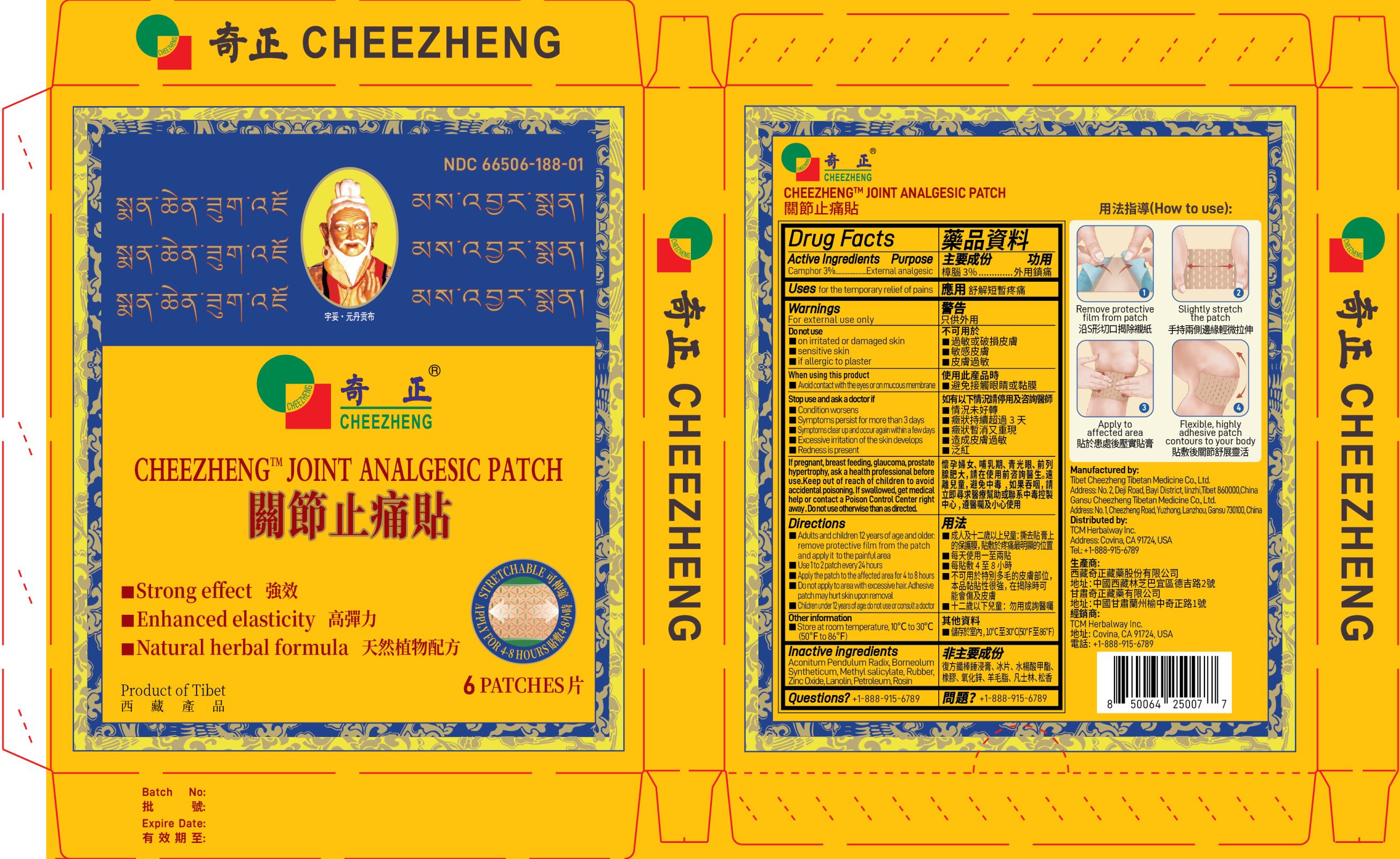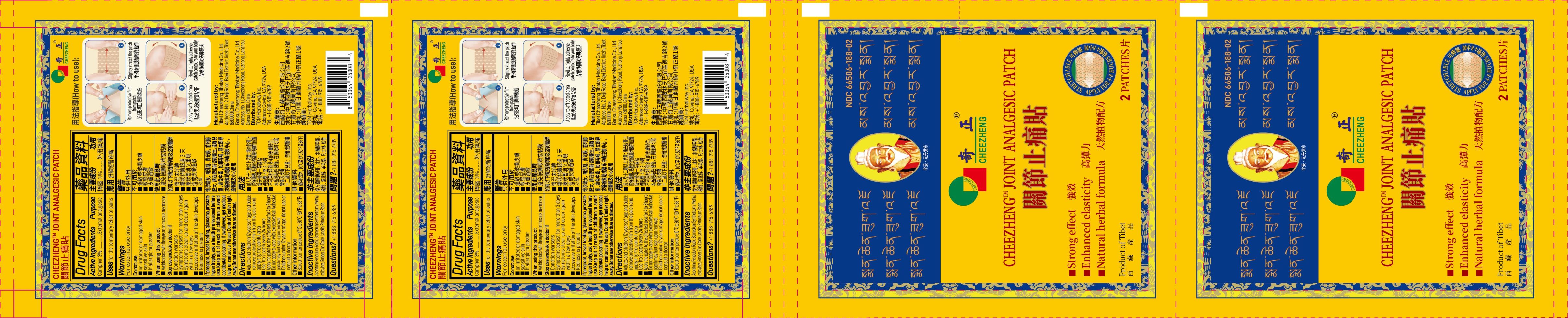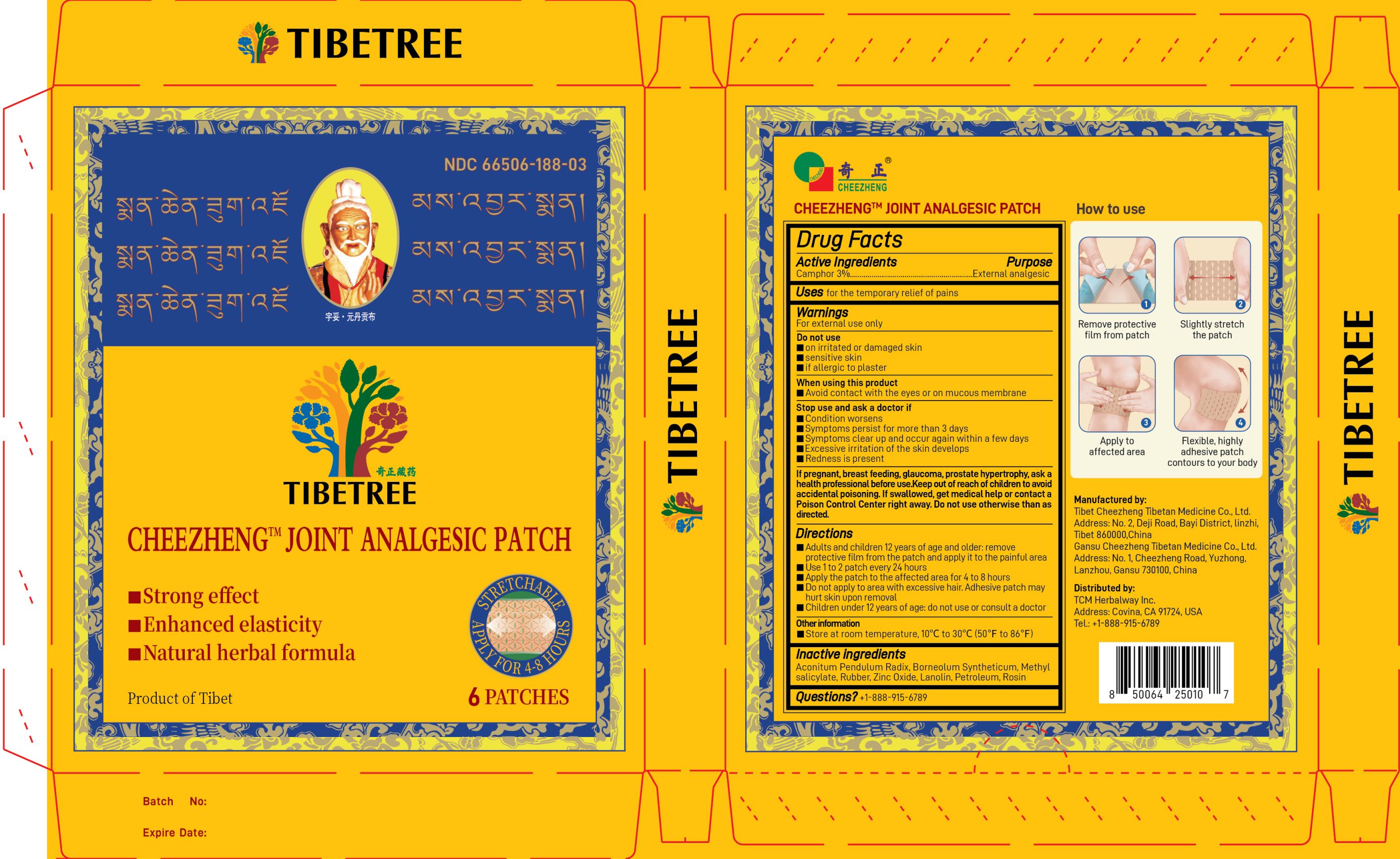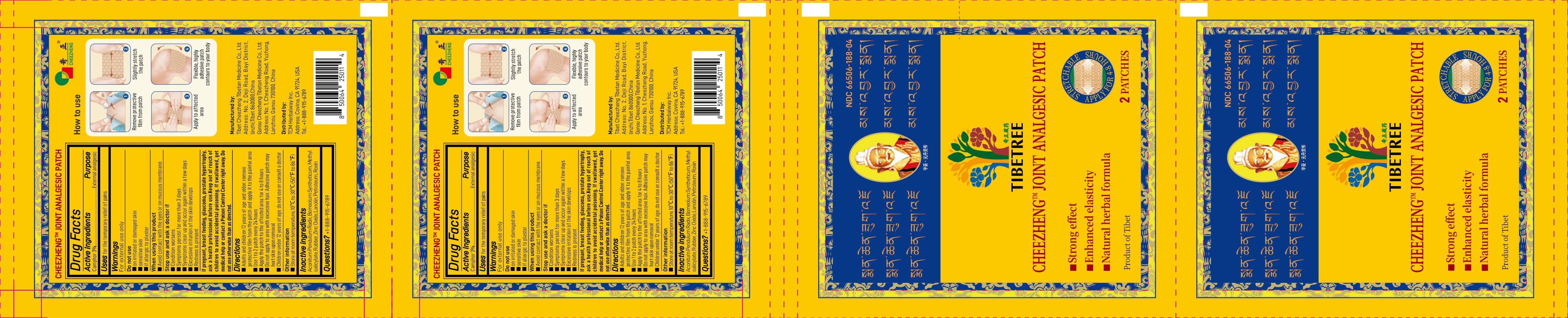 DRUG LABEL: Tibetree Cheezheng Joint Analgesic Patch
NDC: 66506-188 | Form: PATCH
Manufacturer: Tibet Cheezheng Tibetan Medicine Co. Ltd
Category: otc | Type: HUMAN OTC DRUG LABEL
Date: 20240920

ACTIVE INGREDIENTS: CAMPHOR (NATURAL) 3 g/100 g
INACTIVE INGREDIENTS: ACONITUM PENDULUM ROOT; BORNEOL; METHYL SALICYLATE; NATURAL LATEX RUBBER; ZINC OXIDE; LANOLIN; PETROLATUM; ROSIN

Tibetree Cheezheng Joint Analgesic Patch

Active ingredients

Camphor 3%.................……….…….External analgesic

Do not use otherwise than as directed

Keep out of reach of children to avoid accidental poisoning. If swallowed, get medical help or contact a Poison Control Center right away.

If pregnant

If pregnant, breast feeding, glaucoma, prostate hypertrophy, ask a health professional before use

Directions

- Adults and children 12 years of age and older: remove protective film from the patch and apply it to the painful area
- Use 1 to 2 plasters every 24 hours
- Apply the patch to the affected area for 4 to 8 hours
- Do not apply to area with excessive hair. Adhesive patch may hurt skin upon removal.
- Children under 12 years of age: do not use or consult a doctor

Other information

store at room temperature, 10° to 30°C(50°F to 86°F)

Inactive ingredients

Aconitum Pendulum Radix. Borneolum Syntheticum, Methyl salicylate, Rubber, Zinc Oxide, Lanolin, Petroleum, Rosin

Questions?

1-888-915-6789

Purpose

External analgesic

Do not use

- on irritated or damaged skin
- sensitive skin
- if allergic to plaster

When using this product

- Avoid contact with the eyes or on mucous membrane

Stop use and ask a doctor if

- Condition worsens
- Symptoms persist for more than 3 days
- Symptoms clear up and occur again within a few days
- Excessive irritation of the skin develops
- Redness is present

Uses

For the temporary relief of pains

Warnings

For external use only